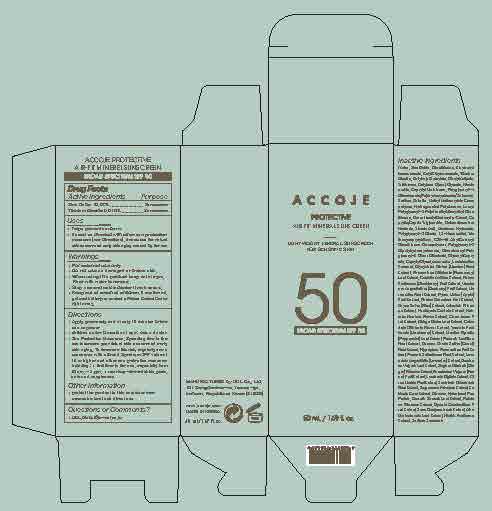 DRUG LABEL: ACCOJE PROTECTIVE AIR-FIT MINERAL SUNSCREEN
NDC: 70574-100 | Form: LOTION
Manufacturer: UCL Co., Ltd.
Category: otc | Type: HUMAN OTC DRUG LABEL
Date: 20260112

ACTIVE INGREDIENTS: ZINC OXIDE 10.08 g/100 mL; TITANIUM DIOXIDE 5.616 g/100 mL
INACTIVE INGREDIENTS: SARGASSUM FULVELLUM; WATER; SARGASSUM FUSIFORME; ALOE BARBADENSIS LEAF; SODIUM SUCCINATE; DIMETHICONE; CENTELLA ASIATICA TRITERPENOIDS; BLUEBERRY; MENTHA PIPERITA LEAF; HIPPOPHAE RHAMNOIDES FRUIT; PAEONIA SUFFRUTICOSA ROOT; BAMBUSA VULGARIS LEAF; BLACKBERRY; CAMELLIA SINENSIS LEAF; CITRUS JUNOS FRUIT; PAEONIA LACTIFLORA ROOT; CARROT; BENZOTRIAZOLYL DODECYL P-CRESOL; CAPRYLIC/CAPRIC TRIGLYCERIDE; DISTEARDIMONIUM HECTORITE; DIISOSTEAROYL POLYGLYCERYL-3 DIMER DILINOLEATE; POMEGRANATE; ARTEMISIA PRINCEPS WHOLE; HOUTTUYNIA CORDATA FLOWERING TOP; TANGERINE PEEL; POLYGLYCERYL-2 DIPOLYHYDROXYSTEARATE; POLYGLYCERYL-4 DIISOSTEARATE/POLYHYDROXYSTEARATE/SEBACATE; GINGER; FOENICULUM VULGARE FRUIT; LAMINARIA DIGITATA; CETYL ETHYLHEXANOATE; BUTYLOCTYL SALICYLATE; DIBUTYL ADIPATE; GLYCYRRHIZA GLABRA (LICORICE) ROOT; ROSEMARY; APPLE; ADENOSINE; LIMOSILACTOBACILLUS FERMENTUM; CAPRYLYL METHICONE; SODIUM CHLORIDE; C30-45 ALKYL CETEARYL DIMETHICONE CROSSPOLYMER; GLYCERYL CAPRYLATE; CAPRYLYL GLYCOL; MORUS ALBA ROOT; POLYGLYCERYL-3 OLEATE; ETHYLHEXYL ISONONANOATE; LAVANDULA ANGUSTIFOLIA FLOWERING TOP; TRISILOXANE; METHYL METHACRYLATE/GLYCOL DIMETHACRYLATE CROSSPOLYMER; LAURYL POLYGLYCERYL-3 POLYDIMETHYLSILOXYETHYL DIMETHICONE (4000 MPA.S); BUTYLENE GLYCOL; GLYCERIN; NIACINAMIDE; SCUTELLARIA BAICALENSIS ROOT; ECKLONIA CAVA; RICE GERM; NELUMBO NUCIFERA FLOWER; CALENDULA OFFICINALIS FLOWER; PEA PROTEIN; PURSLANE; GLUCOSE; HYDROGENATED POLYDECENE TYPE I; STEARIC ACID; ALUMINUM HYDROXIDE; 1,2-HEXANEDIOL; TRIETHOXYCAPRYLYLSILANE; GINKGO; TREMELLA FUCIFORMIS FRUITING BODY; OPUNTIA COCHENILLIFERA FRUIT

ACCOJE PROTECTIVE AIR-FIT MINERAL SUNSCREEN

Active ingredients

Titanium Dioxide 5.616%

Zinc Oxide 10.08

Purpose

Sunscreen

Uses

- Helps prevent sunburn

- If used as directed with other sun protection measures (see Directions), decrease the risk of skin cancer and early skin aging caused by the sun.

Warnings

- For external use only

- Do not use on damaged or broken skin.

- When using this product keep out of eyes. Rinse with water to remove.

- Stop use and ask a doctor if rash occurs.

- Keep out of reach of children. If swallowed, get medical help or contact a Poison Control Center right away.

Directions

- Apply generously and evenly 15 minutes before sun exposure

- Children under 6 months of age: Ask a doctor

- Sun Protection Measures. Spending time in the sun increases your risk of skin cancer and early skin aging. To decrease the risk, regularly use a sunscreen with a Broad Spectrum SPF value of 15 or higher and other sun protection measures including:

- limit time in the sun, especially from 10 a.m. - 2 p.m.

- wear long-sleeved shirts, pants, hats, and sunglasses

Keep out of reach of children

If swallowed, get medical help or contact a Poison Control Center right away

Inactive ingredients

Water, Dimethicone, Ethylhexyl Isononanoate, Cetyl Ethylhexanoate, Butyloctyl Salicylate, Dibutyl Adipate, Trisiloxane, Butylene Glycol, Glycerin, Niacinamide, Caprylyl Methicone, Polyglyceryl-4 Diisostearate/Polyhydroxystearate/Sebacate, Sodium Chloride, Methyl Methacrylate Crosspolymer, Hydrogenated Polydecene, Lauryl Polyglyceryl-3 Polydimethylsiloxyethyl Dimethicone, Benzotriazolyl Dodecyl p-Cresol, Caprylic/Capric Triglyceride, Disteardimonium Hectorite, Stearic Acid, Aluminum Hydroxide, Polyglyceryl-3 Oleate, 1,2-Hexanediol, Triethoxycaprylylsilane, C30-45 Alkyl Cetearyl Dimethicone Crosspolymer, Polyglyceryl-2 Dipolyhydroxystearate, Diisostearoyl Polyglyceryl-3 Dimer Dilinoleate, Glyceryl Caprylate, Caprylyl Glycol, Adenosine, Lactobacillus Ferment, Glycyrrhiza Glabra (Licorice) Root Extract, Rosmarinus Officinalis (Rosemary) Leaf Extract, Centella Asiatica Extract, Rubus Fruticosus (Blackberry) Fruit Extract, Vaccinium Angustifolium (Blueberry) Fruit Extract, Morus Alba Root Extract, Pyrus Malus (Apple) Fruit Extract, Punica Granatum Fruit Extract, Oryza Sativa (Rice) Extract, Artemisia Princeps Extract, Houttuynia Cordata Extract, Nelumbo Nucifera Flower Extract, Citrus Junos Fruit Extract, Ginkgo Biloba Leaf Extract, Calendula Officinalis Flower Extract, Tremella Fuciformis (Mushroom) Extract, Mentha Piperita (Peppermint) Leaf Extract, Paeonia Lactiflora Root Extract, Daucus Carota Sativa (Carrot) Root Extract, Hippophae Rhamnoides Fruit Extract, Paeonia Suffruticosa Root Extract, Lavandula Angustifolia (Lavender) Extract, Bambusa Vulgaris Leaf Extract, Zingiber Officinale (Ginger) Rhizome Extract, Foeniculum Vulgare (Fennel) Fruit Extract, Laminaria Digitata Extract, Citrus Unshiu Peel Extract, Scutellaria Baicalensis Root Extract, Sargassum Fulvellum Extract, Ecklonia Cava Extract, Glucose, Hydrolyzed Pea Protein, Camellia Sinensis Leaf Extract, Portulaca Oleracea Extract, Opuntia Coccinellifera Fruit Extract, Sasa Quelpaertensis Extract, Aloe Barbadensis Leaf Extract, Hizikia Fusiforme Extract, Sodium Succinate